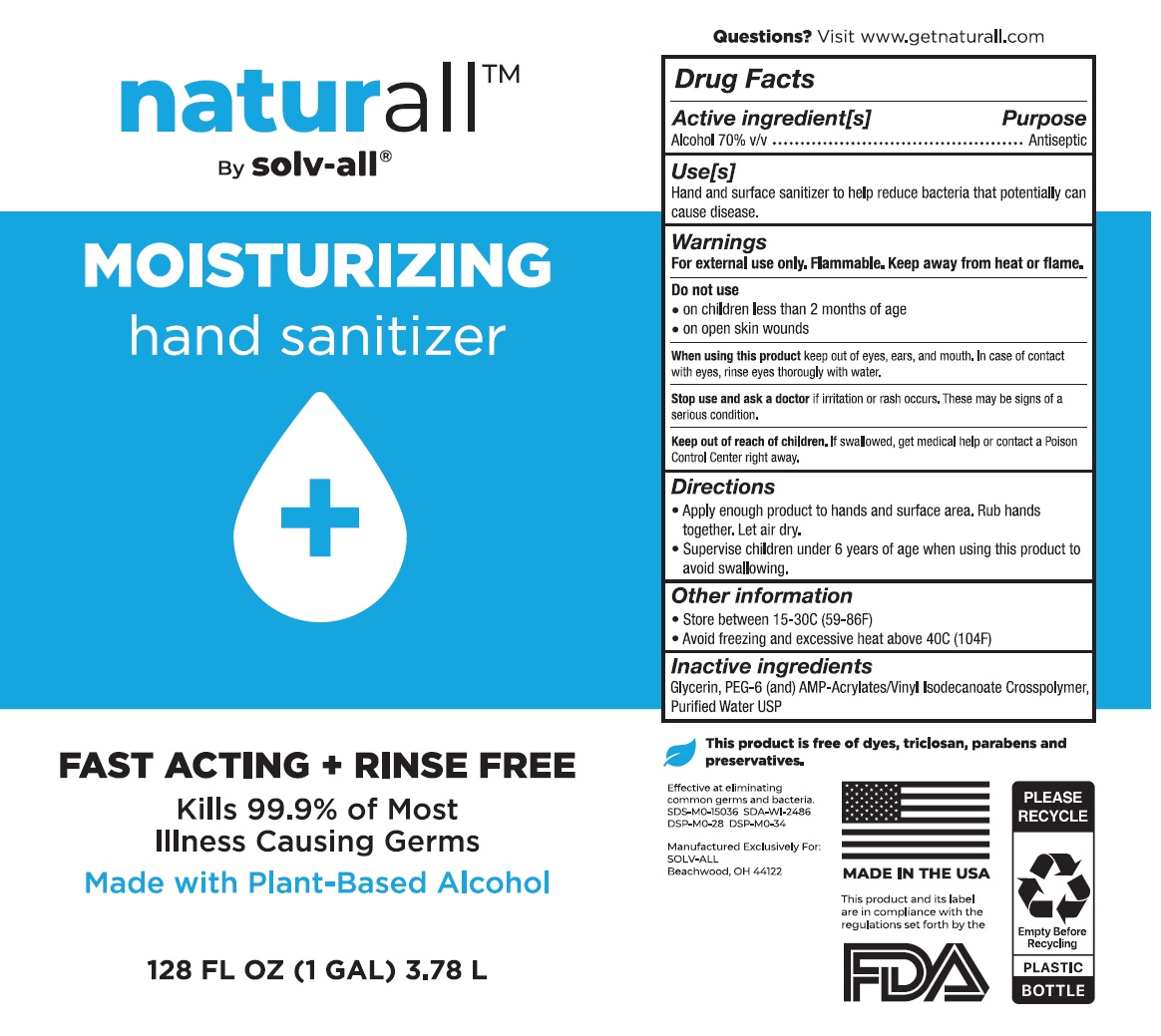 DRUG LABEL: naturall MOISTURIZING hand sanitizer
NDC: 77023-070 | Form: GEL
Manufacturer: Solv-All Alliance Group, LLC
Category: otc | Type: HUMAN OTC DRUG LABEL
Date: 20201001

ACTIVE INGREDIENTS: ALCOHOL 70 mL/100 mL
INACTIVE INGREDIENTS: GLYCERIN; POLYETHYLENE GLYCOL 300; ACRYLATES/VINYL ISODECANOATE CROSSPOLYMER (10000 MPA.S NEUTRALIZED AT 0.5%); WATER

naturall™ MOISTURIZING hand sanitizer

Active ingredient[s]

Alcohol 70% v/v

Purpose

Antiseptic

Use[s]

Hand and surface sanitizer to help reduce bacteria that potentially can cause disease.

Warnings

For external use only. Flammable. Keep away from heat or flame.

Do not use

• on children less than 2 months of age

• on open skin wounds

When using this product keep out of eyes, ears, and mouth. In case of contact with eyes, rinse eyes thoroughly with water.

Stop use and ask a doctor if irritation or rash occurs. These may be signs of a serious condition.

Keep out of reach of children. If swallowed, get medical help or contact a Poison Control Center right away.

Directions

• Apply enough product to hands and surface area. Rub hands together. Let air dry.

• Supervise children under 6 years of age when using this product to avoid swallowing.

Other information

• Store between 15-30C (59-86F)

• Avoid freezing and excessive heat above 40C (104F)

Inactive ingredients

Glycerin, PEG-6 (and) AMP-Acrylates/Vinyl Isodecanoate Crosspolymer, Purified Water USP